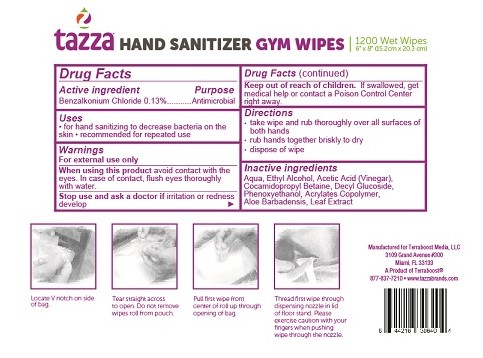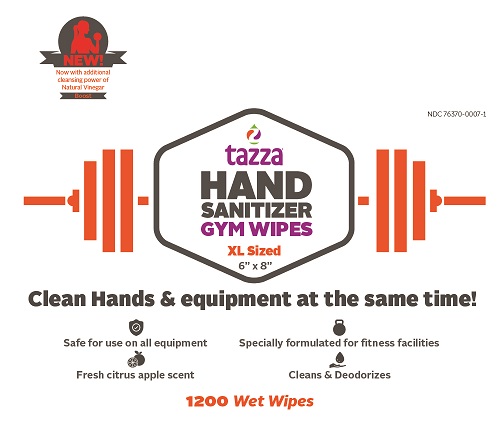 DRUG LABEL: Tazza
NDC: 76370-0007 | Form: CLOTH
Manufacturer: Tazza Brands East Inc.
Category: otc | Type: HUMAN OTC DRUG LABEL
Date: 20250101

ACTIVE INGREDIENTS: BENZALKONIUM CHLORIDE 0.0062 g/1 1
INACTIVE INGREDIENTS: ACETIC ACID; COCAMIDOPROPYL BETAINE; PHENOXYETHANOL; ALOE VERA LEAF; BUTYL ACRYLATE/METHYL METHACRYLATE/METHACRYLIC ACID COPOLYMER (18000 MW); WATER; ALCOHOL; DECYL GLUCOSIDE

Tazza Hand Sanitizing Gym Wipes

Drug Facts

Active ingredient

Benzalkonium Chloride 0.13%

Purpose

Antimicrobial

Uses

- for hand sanitizing to decrease bacteria on the skin
- recommended for repeated use

Warnings

For external use only

When using this product avoid contact with eyes. In case of eye contact, flush eyes with water.

Stop use and ask a doctor if irritation or redness develop

Keep out of reach of children. If swallowed, get medical help or contact a Poison Control Center right away.

Directions

- take wipe and rub thoroughly over all surfaces of both hands
- rub hands together briskly to dry
- dispose of wipe

INACTIVE INGREDIENT

Inactive ingredients Aqua, Ethyl Alcohol, Acetic Acid (Vinegar), Cocamidopropyl Betaine, Decyl Glucoside, Phenoxyethanol, Acrylates Copolymer, Aloe Barbadensis Leaf Extract,

Manufactured for Terraboost Media, LLC

3109 Grand Avenue #300

Miami, FL 33133

877-837-7210

A Product of Terraboost®

877-837-7210

www.tazzabrands.com

PACKAGE LABEL

NEW! Now with the additional cleansing power of Natural Vinegar

NDC 76370-0007-1

tazza®

HAND SANITIZER GYM WIPES

XL Sized

6" x 8"

Clean Hands & equipment at the same time!

Safe for use on all equipment

Specially formulated for fitness facilities

Fresh citrus apple scent

Cleans and deodorizes

1200 Wet Wipes